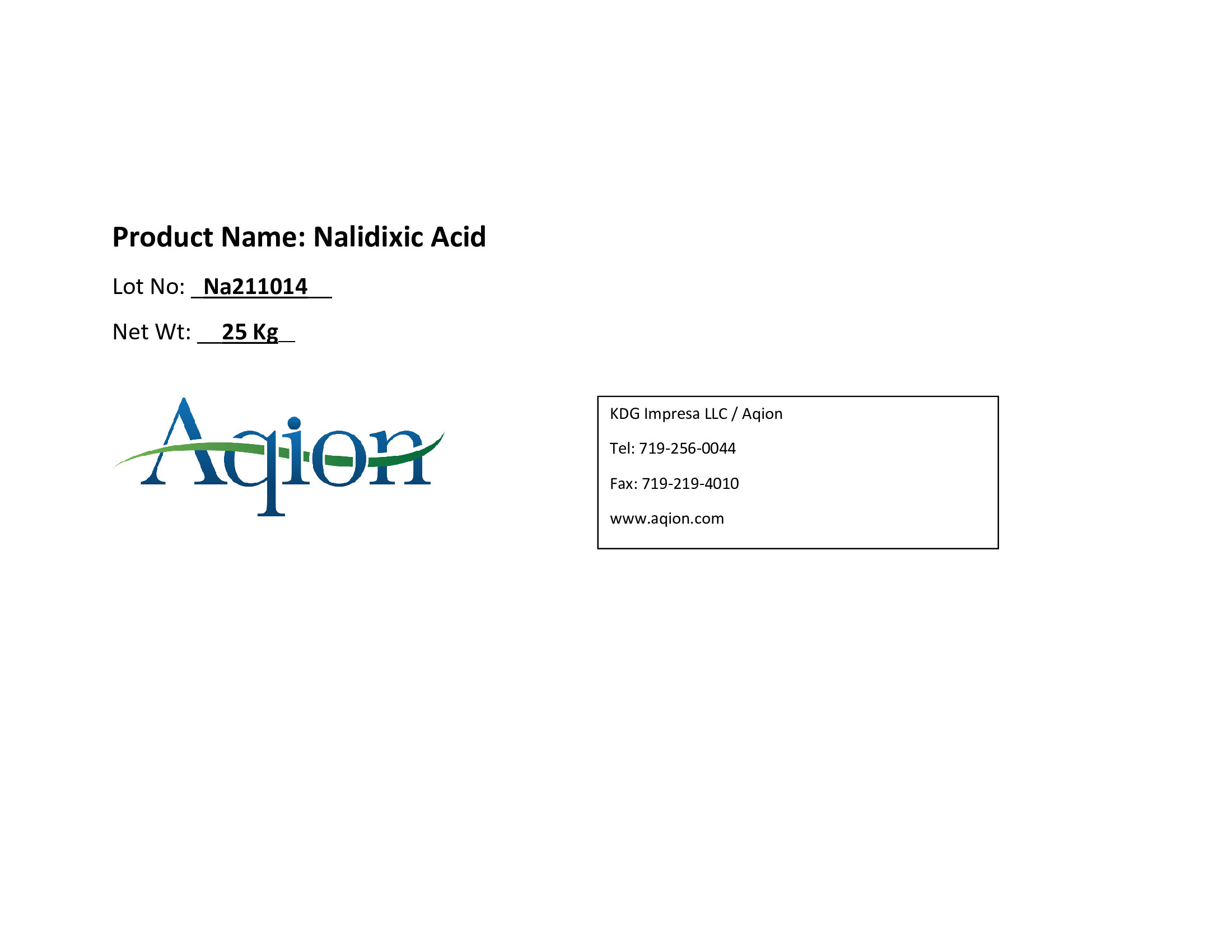 DRUG LABEL: Nalidixic Acid
NDC: 43457-542 | Form: POWDER
Manufacturer: KDG Impresa LLC, Aqion
Category: other | Type: BULK INGREDIENT - ANIMAL DRUG
Date: 20220223

ACTIVE INGREDIENTS: NALIDIXIC ACID 1 kg/1 kg

Nalidixic Acid